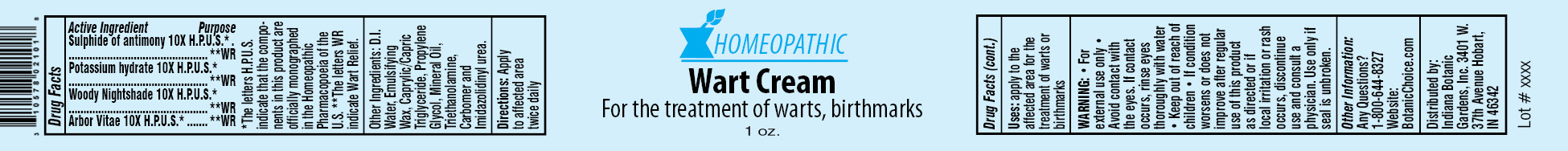 DRUG LABEL: Homeopathic Wart
NDC: 10578-021 | Form: CREAM
Manufacturer: Indiana Botanic Gardens
Category: homeopathic | Type: HUMAN OTC DRUG LABEL
Date: 20120427

ACTIVE INGREDIENTS: ANTIMONY TRISULFIDE 10 [hp_X]/28 g; CAUSTICUM 10 [hp_X]/28 g; SOLANUM DULCAMARA TOP 10 [hp_X]/28 g; THUJA OCCIDENTALIS LEAFY TWIG 10 [hp_X]/28 g
INACTIVE INGREDIENTS: WATER; CETOSTEARYL ALCOHOL; POLYSORBATE 60; TRICAPRYLIN; PROPYLENE GLYCOL; MINERAL OIL; TROLAMINE; CARBOMER 934; IMIDUREA

Homeopathic Wart Cream

Active Ingredients

Sulphide of antimony 10X H.P.U.S.*

Potassium hydrate 10X H.P.U.S.*

Woody Nightshade 10X H.P.U.S.*

Arbor Vitae 10X H.P.U.S.*

Purpose

**WR

**WR

**WR

**WR

*The letters H.P.U.S. indicate that the components in this product are officially monographed in the Homeopathic Pharmacopoeia of the U.S. **The letters WR indicate Wart Relief.

Other Ingredients:

D.I. Water, Emulsifying Wax, Caprylic/Capric Triglyceride, Propylene Glycol, Mineral Oil, Triethanolamine, Carbomer and Imidazolidinyl urea.

Directions:

Apply to affected area twice daily

Uses:

apply to the affected area for the treatment of warts or birthmarks

WARNING:

- for external use only
- Avoid contact with the eyes. If contact occurs, rinse eyes thoroughly with water

- Keep out of reach of children

STOP USE

- If condition worsens or does not improve after regular use of this product as directed or if local irritation or rash occurs, discontinue use and consult a physician.

Use only if seal is unbroken.

Other Information:

Any Questions?

1-800-644-8327

Website:

BotanicChoice.com

Distributed by:

Indiana Botanic Gardens, Inc. 3401 W. 37th Avenue Hobart, IN 46342

Homeopathic Wart Cream

For the treatment of warts, birthmarks

1 oz.